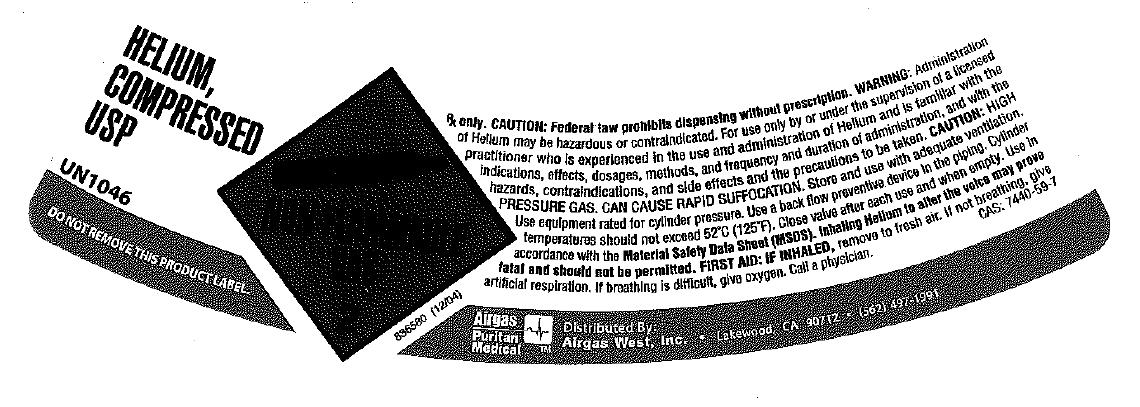 DRUG LABEL: Helium
NDC: 10678-004 | Form: GAS
Manufacturer: Airgas-West, Inc.
Category: prescription | Type: HUMAN PRESCRIPTION DRUG LABEL
Date: 20100525

ACTIVE INGREDIENTS: Helium 992 mL/1 L

helium

PACKAGE LABEL

HELIUM, COMPRESSED USP
UN1046
DO NOT REMOVE THIS PRODUCT LABEL.
NON-FLAMMABLE 2
836580 (12/04)
Rx only.
CAUTION: Federal law prohibits dispensing without a prescription. WARNING: Administration of Helium may be hazardous or contraindicated. For use by or under the supervision of a licensed practitioner who is experienced in the use and administration of Helium and is familiar with the indications, effects, dosages, methods, and frequency and duration of administration, and with the hazards, contraindications and side effects, and the precautions to be taken.
CAUTION: HIGH PRESSURE GAS. CAN CAUSE RAPID SUFFOCATION. Store and use with adequate ventilation. Use only with equipment rated for cylinder pressure. Use a back flow preventive device in the piping. Cylinder temperature should not exceed 52oC(125oF). Close valve after each use and when empty. Use in accordance with the Material Safety Data Sheet (MSDS). Inhaling Helium to alter the voice may prove fatal and should not be permitted.
FIRST AID: IF INHALED, remove to fresh air. If not breathing, give artificial respiration. If breathing is difficult, give oxygen. Call a physician. CAS: 7440-59-7
AIRGAS PURITAN MEDICAL Distributed By: Airgas West, Inc. Lakewood, CA 90712 (562) 497-1991